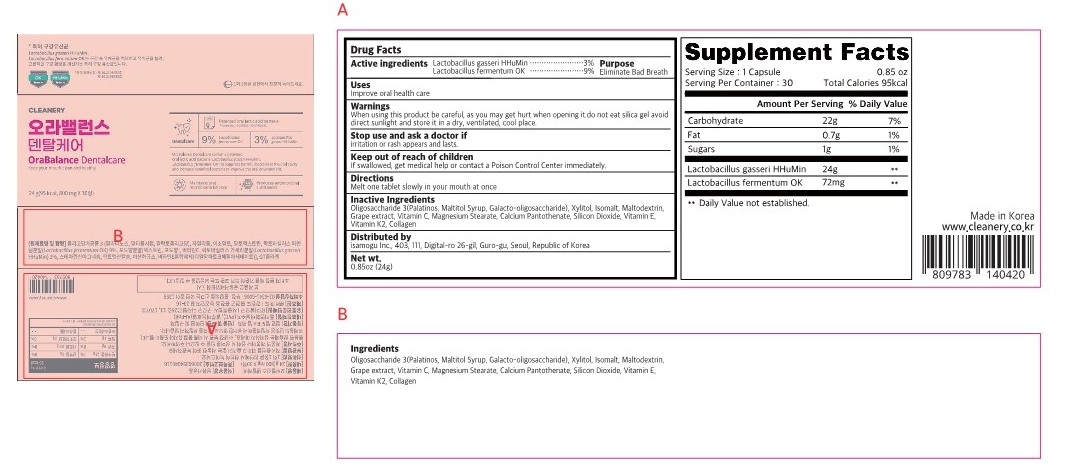 DRUG LABEL: OraBalance dentalcare
NDC: 82690-401 | Form: TABLET
Manufacturer: isamogu Inc.
Category: otc | Type: HUMAN OTC DRUG LABEL
Date: 20220713

ACTIVE INGREDIENTS: LACTOBACILLUS GASSERI 24 mg/100 g; LIMOSILACTOBACILLUS FERMENTUM 72 mg/100 g
INACTIVE INGREDIENTS: MENAQUINONE 6; COLLAGEN, SOLUBLE, FISH SKIN; CALCIUM PANTOTHENATE; CITRUS PARADISI WHOLE; SILICON DIOXIDE; ALPHA-TOCOPHEROL; ISOMALTULOSE ANHYDROUS; 4'-GALACTOSYLLACTOSE; MALTITOL; XYLITOL; ISOMALT; MALTODEXTRIN; ASCORBIC ACID; MAGNESIUM STEARATE

82690-401
OraBalance Dentalcare

Active ingredients

Lactobacillus gasseri HHuMin

Lactobacillus fermentum OK

Purpose

Eliminate Bad Breath

use

Improve oral health care

Warnings

do not eat silica gel

Warnings

be careful, as you may get hurt when opening it.

Warnings

Stop use and ask a doctor if irritation or rash appears and lasts.

Warnings

avoid direct sunlight and store it in a dry, ventilated, cool place.

Warnings

Keep out of reach of children

Directions

Melt one tablet slowly in your mouth and eat once

Inactive Ingredients

Oligosaccharide 3(Palatinos, Maltitol Syrup, Galacto-oligosaccharide)
xylitol
isomalt
maltodextrin
grape flavor powder
vitamin C
Magnesium Stearate
Calcium Pantothenate
silicon dioxide
vitamin E
vitamin K2
collagen

PACKAGE LABEL

82690-401
OraBalance Dentalcare